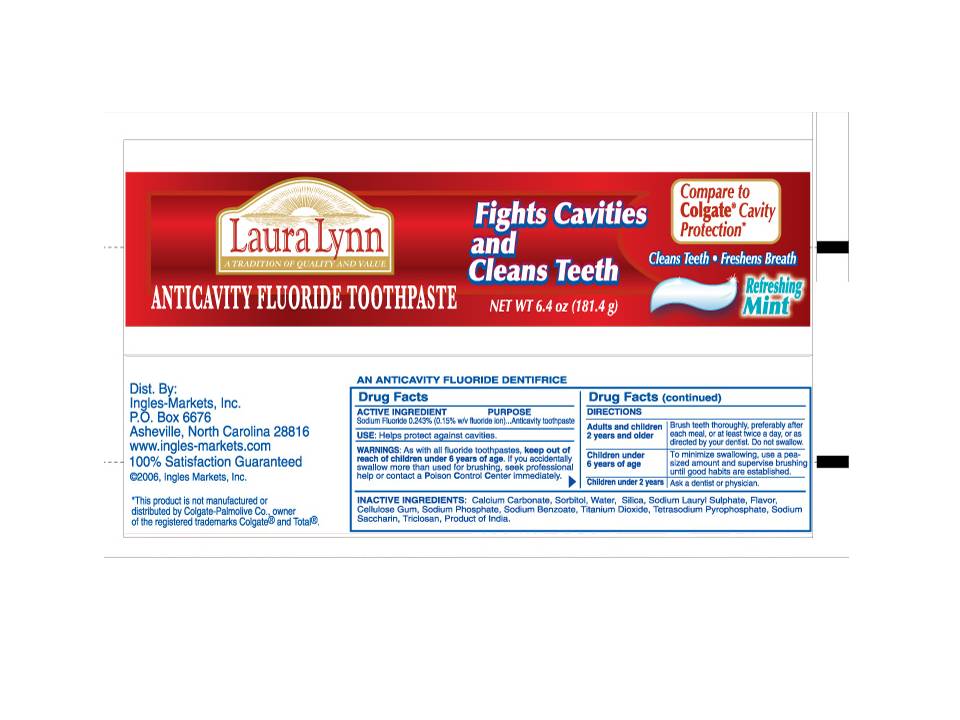 DRUG LABEL: Laura Lynn Anticavity 
NDC: 67659-041 | Form: PASTE
Manufacturer: Team Technologies, Inc
Category: otc | Type: HUMAN OTC DRUG LABEL
Date: 20101130

ACTIVE INGREDIENTS: SODIUM FLUORIDE 2.43 mg/1 g
INACTIVE INGREDIENTS: SORBITOL; WATER; HYDRATED SILICA; SODIUM LAURYL SULFATE; CARBOXYMETHYLCELLULOSE SODIUM ; SODIUM PHOSPHATE; SODIUM BENZOATE; TITANIUM DIOXIDE; SODIUM PYROPHOSPHATE; SACCHARIN SODIUM; TRICLOSAN

Laura Lynn Anticavity Fluoride Toothpaste

Active Ingredient

SODIUM FLUORIDE 0.243% (0.15% WITH FLUORIDE ION)...ANTICAVITY TOOTHPASTE

USE

Helps protect against cavities

WARNINGS

As with all fluoride toothpastes, keep out of reach of children under 6 years of age. If you accidentally swallow more than used for brushing, seek professional help or contact a Poison Control Center immediately.

Directions

Adults and children Brush teeth thoroughly, preferably after
2 years and older each meal, or at least twice a day, or as
directed by your dentist. Do not swallow.
Children under To minimize swallowing, use a pea-
6 years and older sized amount and supervise brushing
until good habits are established.
Children under 2 years Ask a dentist or physician.

Inactive ingredients:

Calcium Carbonate, Soribitol, Water, Hydrated Silica, Sodium Lauryl Sulphate, Flavor, Cellulose Gum, Sodium Phosphate, Sodium Benzoate, Titanium Dioxide, Tetrasodium Pyrophosphate, Sodium Saccharin, Triclosan